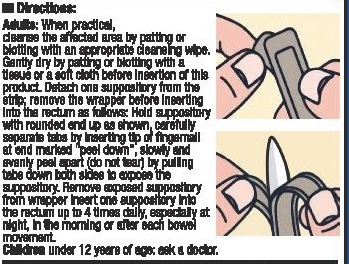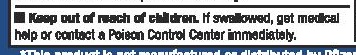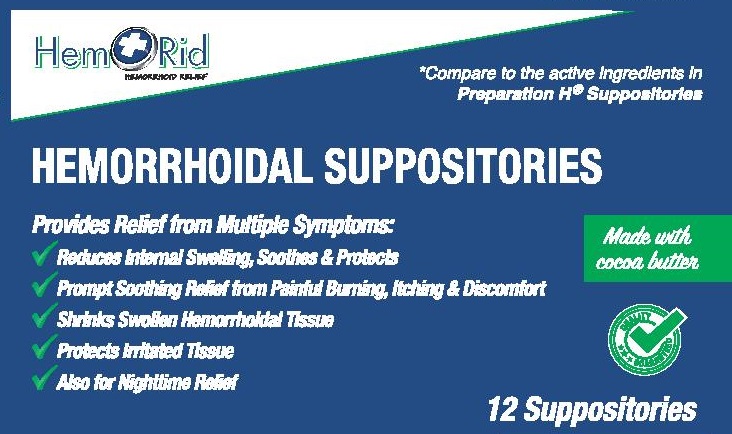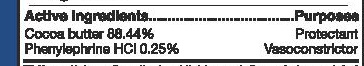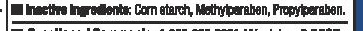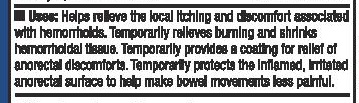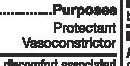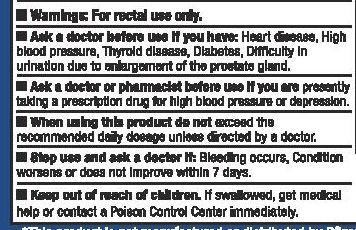 DRUG LABEL: Hem Rid
NDC: 71430-200 | Form: SUPPOSITORY
Manufacturer: Belligadria Sollutions LLC
Category: otc | Type: HUMAN OTC DRUG LABEL
Date: 20191225

ACTIVE INGREDIENTS: COCOA BUTTER 88.44 g/100 g; PHENYLEPHRINE HYDROCHLORIDE 0.25 g/100 g
INACTIVE INGREDIENTS: MODIFIED CORN STARCH (1-OCTENYL SUCCINIC ANHYDRIDE); METHYLPARABEN; PROPYLPARABEN

HemRid Hemorrhoidal Suppositories 12 ct